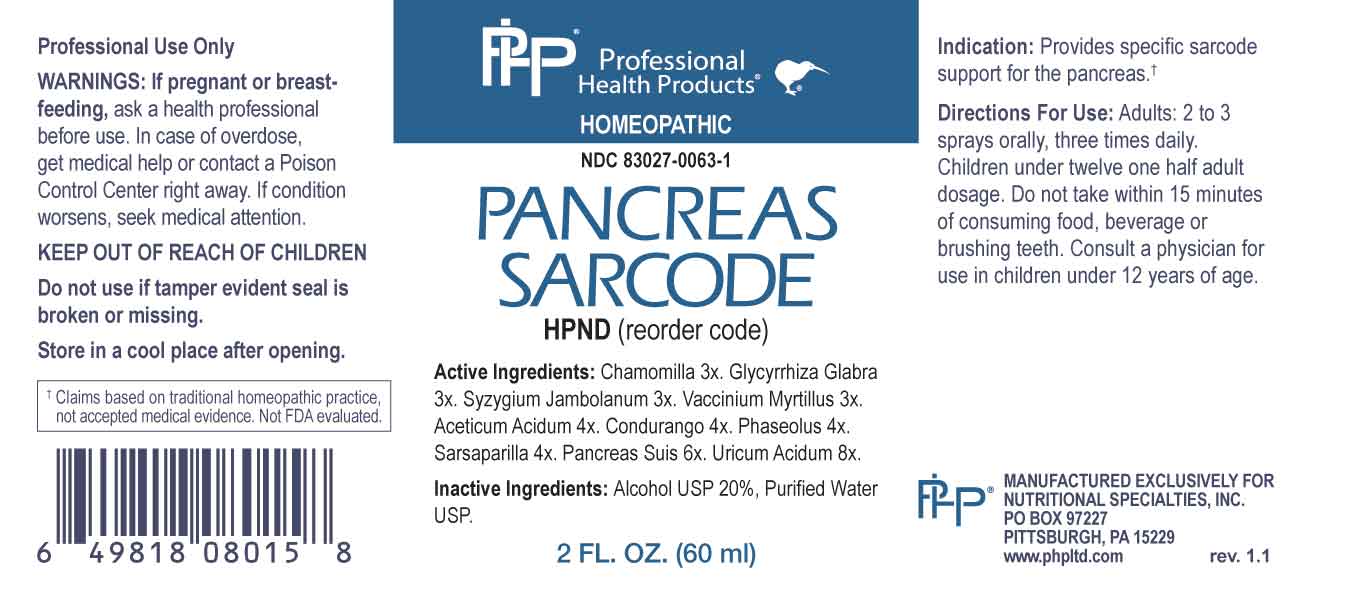 DRUG LABEL: Pancreas Sarcode
NDC: 83027-0063 | Form: SPRAY
Manufacturer: Nutritional Specialties, Inc.
Category: homeopathic | Type: HUMAN OTC DRUG LABEL
Date: 20230925

ACTIVE INGREDIENTS: MATRICARIA CHAMOMILLA WHOLE 3 [hp_X]/1 mL; GLYCYRRHIZA GLABRA 3 [hp_X]/1 mL; SYZYGIUM CUMINI SEED 3 [hp_X]/1 mL; BILBERRY 3 [hp_X]/1 mL; ACETIC ACID 4 [hp_X]/1 mL; RUEHSSIA CUNDURANGO BARK 4 [hp_X]/1 mL; KIDNEY BEAN 4 [hp_X]/1 mL; SMILAX ORNATA ROOT 4 [hp_X]/1 mL; SUS SCROFA PANCREAS 6 [hp_X]/1 mL; URIC ACID 8 [hp_X]/1 mL
INACTIVE INGREDIENTS: WATER; ALCOHOL

DRUG FACTS:

ACTIVE INGREDIENTS:

Chamomilla 3X, Glycyrrhiza Glabra 3X, Syzygium Jambolanum 3X, Vaccinium Myrtillus 3X, Aceticum Acidum 4X, Condurango 4X, Phaseolus 4X, Sarsaparilla 4X, Pancreas Suis 6X, Uricum Acidum 8X.

PURPOSE:

Provides specific sarcode support for the pancreas.†

†Claims based on traditional homeopathic practice, not accepted medical evidence. Not FDA evaluated.

WARNINGS:

Professional Use Only

If pregnant or breast-feeding, ask a health professional before use.

In case of overdose, get medical help or contact a Poison Control Center right away.

If condition worsens, seek medical attention.

KEEP OUT OF REACH OF CHILDREN

Do not use if tamper evident seal is broken or missing.

Store in a cool place after opening

KEEP OUT OF REACH OF CHILDREN:

In case of overdose, get medical help or contact a Poison Control Center right away.

DIRECTIONS:

Adults: 2 to 3 sprays orally, three times daily. Children under twelve one half adult dosage. Do not take within 15 minutes of consuming food, beverage or brushing teeth. Consult a physician for use in children under 12 years of age.

INDICATIONS:

Provides specific sarcode support for the pancreas.†

†Claims based on traditional homeopathic practice, not accepted medical evidence. Not FDA evaluated.

INACTIVE INGREDIENTS:

Alcohol USP 20%, Purified Water USP.

QUESTIONS:

MANUFACTURED EXCLUSIVELY FOR

NUTRITIONAL SPECIALTIES, INC.

PO BOX 97227

PITTSBURG, PA 15229

www.phpltd.com

PACKAGE LABEL DISPLAY:

Professional

Health Products

HOMEOPATHIC

NDC 83027-0063-1

PANCREAS

SARCODE

2 FL. OZ (60 ml)